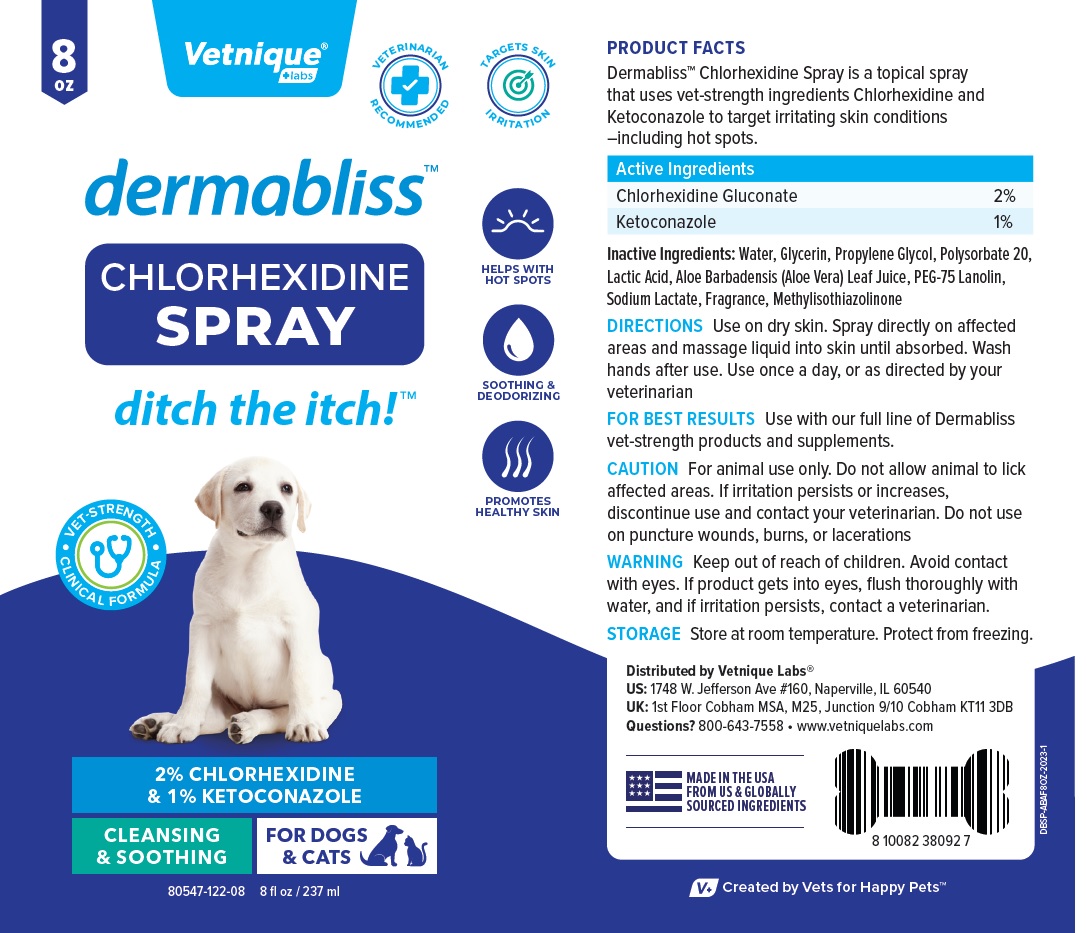 DRUG LABEL: dermabliss
NDC: 80547-122 | Form: SPRAY
Manufacturer: Vetnique Labs LLC
Category: animal | Type: OTC ANIMAL DRUG LABEL
Date: 20230811

ACTIVE INGREDIENTS: CHLORHEXIDINE GLUCONATE 20 mg/1 mL; KETOCONAZOLE 10 mg/1 mL
INACTIVE INGREDIENTS: WATER; GLYCERIN; PROPYLENE GLYCOL; POLYSORBATE 20; LACTIC ACID, UNSPECIFIED FORM; ALOE VERA LEAF; PEG-75 LANOLIN; SODIUM LACTATE; METHYLISOTHIAZOLINONE

dermabliss™ CHLORHEXIDINE SPRAY

Active Ingredients

Chlorhexidine Gluconate 2%
Ketoconazole 1%

INDICATIONS AND USAGE

PRODUCT FACTS
Dermabliss™ Chlorhexidine Spray is a topical spray that uses vet-strength ingredients Chlorhexidine and Ketoconazole to target irritating skin conditions –including hot spots.

INACTIVE INGREDIENT

Inactive Ingredients: Water, Glycerin, Propylene Glycol, Polysorbate 20, Lactic Acid, Aloe Barbadensis (Aloe Vera) Leaf Juice, PEG-75 Lanolin, Sodium Lactate, Fragrance, Methylisothiazolinone

DOSAGE AND ADMINISTRATION

DIRECTIONS Use on dry skin. Spray directly on affected areas and massage liquid into skin until absorbed. Wash hands after use. Use once a day, or as directed by your veterinarian

FOR BEST RESULTS Use with our full line of Dermabliss vet-strength products and supplements.

PRECAUTIONS

CAUTION For animal use only. Do not allow animal to lick affected areas. If irritation persists or increases, discontinue use and contact your veterinarian. Do not use on puncture wounds, burns, or lacerations

WARNINGS

WARNING Keep out of reach of children. Avoid contact with eyes. If product gets into eyes, flush thoroughly with water, and if irritation persists, contact a veterinarian.

STORAGE Store at room temperature. Protect from freezing.

VETERINARIAN RECOMMENDED

TARGETS SKIN IRRITATION

HELPS WITH HOT SPOTS

SOOTHING & DEODORIZING

PROMOTES HEALTHY SKIN

• VET-STRENGTH • CLINICAL FORMULA

CLEANSING & SOOTHING

FOR DOGS & CATS

Distributed by Vetnique Labs®

US: 1748 W. Jefferson Ave #160, Naperville, IL 60540

UK: 1st Floor Cobham MSA, M25, Junction 9/10 Cobham KT11 3DB

Questions? 800-643-7558 • www.vetniquelabs.com

MADE IN THE USA FROM US & GLOBALLY SOURCED INGREDIENTS

V+ Created by Vets for Happy Pets™